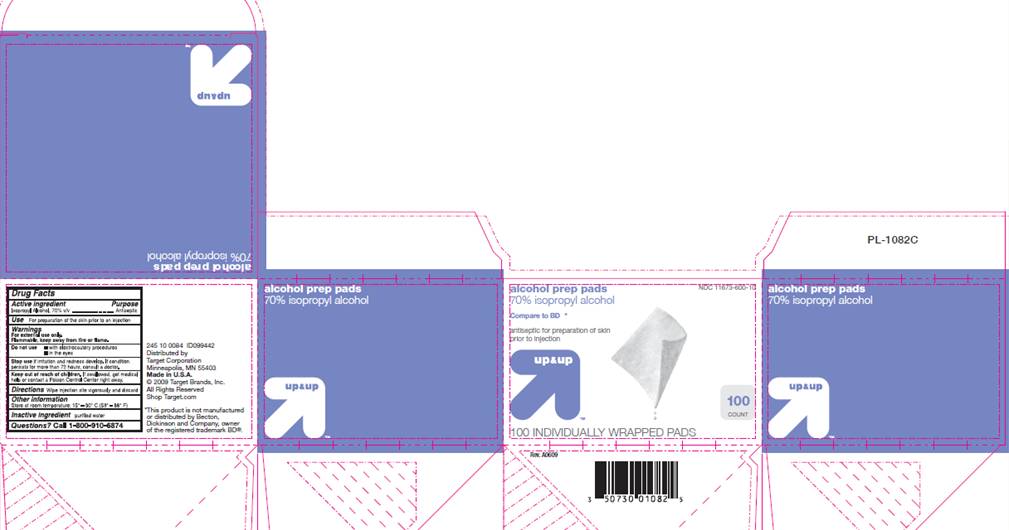 DRUG LABEL: Alcohol Prep Pad
NDC: 11673-600 | Form: SWAB
Manufacturer: Target Corporation
Category: otc | Type: HUMAN OTC DRUG LABEL
Date: 20100201

ACTIVE INGREDIENTS: Isopropyl alcohol 0.70 mL/1 1
INACTIVE INGREDIENTS: water

DRUG FACTS

ACTIVE INGREDIENT

Isopropyl Alcohol 70% v/v

PURPOSE

Antiseptic

USE

For preparation of the skin prior to an injection

WARNINGS

For external use only.
Flammable, keep away from fire or flame.

Do not use

- with electrocautery procedures
- in the eyes

Stop use

if irritation and redness develop. If condition persists for more than 72 hours, consult a doctor.

Keep out of reach of children

If swallowed, get medical help or contact a Poison Control Center right away.

DIRECTIONS

Wipe injection site vigorously and discard.

OTHER INFORMATION

Store at room temperature 15°- 30° C (59° - 86° F)

INACTIVE INGREDIENT

purified water

Questions?

Call 1-800-910-6874

PACKAGE INFORMATION

up and up
NDC 11673-600-10
alcohol prep pads
70% isopropyl alcohol
Compare to BD®*
antiseptic for preparation of skin prior to injection
100 count
100 INDIVIDUALLY WRAPPED PADS
Distributed by Target Corporation
Minneapolis, MN 55403
Made in U.S.A.
© 2009 Target Brands, Inc.
All Rights Reserved
Shop Target.com
*This product is not manufactured or distributed by Becton Dickinson and Company, owner of the registered trademark BD®.